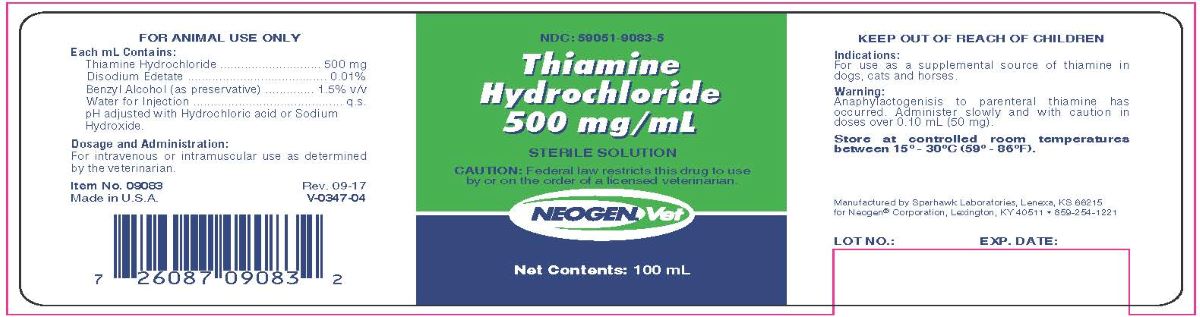 DRUG LABEL: Thiamine Hydrochloride
NDC: 59051-9083 | Form: INJECTION
Manufacturer: Neogen Corporation - Nandino
Category: animal | Type: PRESCRIPTION ANIMAL DRUG LABEL
Date: 20231212

ACTIVE INGREDIENTS: THIAMINE HYDROCHLORIDE 500 mg/1 mL
INACTIVE INGREDIENTS: EDETATE DISODIUM .1 mg/1 mL; BENZYL ALCOHOL .015 mL/1 mL; WATER

Thiamine Hydrochloride
500mg/mL
Sterile Solution

Indications:

For use as a supplemental source of thiamine in dogs, cats, and horses.

Each mL Contains:

Thiamine Hydrochloride..........................500 mg

Disodium Edetate..............................0.01% w/v

Benzyle Alcohol (as preservative)..........1.5% v/v

Water for Injection......................................q.s.

pH adjusted with Hydrochloric acid or Sodium Hydroxide

Dosage and Administration:

For intravenous or intramuscular use as determined by the veterinarian.

Warning:

Anaphylactogenesis to parental thiamine has occurred. Administer slowly and with caution in doses over 0.10 mL (50mg)

STORAGE AND HANDLING

Store at controlled temperatures between 15° and 30°C (59° - 86°F).

Manufactured by Sparhawk Laboratories, Lenexa, KS 66215

for Neogen® Corporation, Lexington, KY 40511 • 859-254-1221

Principal Display Panel

THIAMINE HYDROCHLORIDE

500 mg/mL

Sterile Solution

For use in dogs, cats and horses

Caution: Federal law restricts this drug to use by or on the order of a licensed veterinarian

FOR ANIMAL USE ONLY

KEEP OUT OF THE REACH OF CHILDREN

Net Content:100 mL